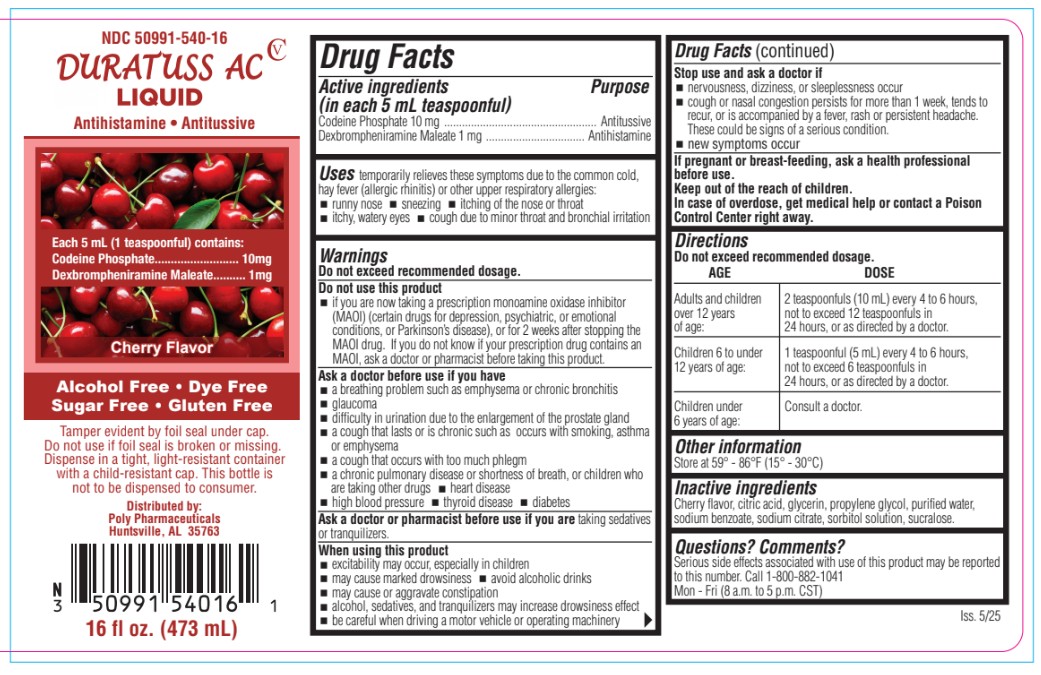 DRUG LABEL: Duratuss AC
NDC: 50991-540 | Form: LIQUID
Manufacturer: Poly Pharmaceuticals, Inc.
Category: otc | Type: HUMAN OTC DRUG LABEL
Date: 20250909
DEA Schedule: CV

ACTIVE INGREDIENTS: CODEINE PHOSPHATE 10 mg/5 mL; DEXBROMPHENIRAMINE MALEATE 1 mg/5 mL
INACTIVE INGREDIENTS: GLYCERIN; ANHYDROUS CITRIC ACID; SORBITOL; WATER; METHYLPARABEN; PROPYLENE GLYCOL; SUCRALOSE; SODIUM CITRATE; SODIUM BENZOATE

Duratuss AC

Active ingredients

(in each 5 mL teaspoonful)

Codeine Phosphate 10 mg ................................................... Antitussive
Dexbrompheniramine Maleate 1 mg ................................. Antihistamine

PURPOSE

Antihistamine

Antitussive

Uses

temporarily relieves these symptoms due to the common cold, hay fever (allergic rhinitis) or other upper respiratory allergies:

- runny nose
- sneezing
- itching of nose or throat
- itchy, watery eyes
- cough due to minor throat and bronchial irritation
- nasal congestion
- reduces swelling of nasal passages

Warnings

Do not exceed recommended dosage.

Ask a doctor or pharmacist before use if you are taking sedatives or tranquilizers.

Ask a doctor before use if you have

- a breathing problem such as emphysema or chronic bronchitis
- glaucoma
- difficulty in urination due to the enlargement of the prostate gland
- a cough that lasts or is chronic such as occurs with smoking, asthma or emphysema
- a cough that occurs with too much phlegm
- a chronic pulmonary disease or shortness of breath, or children who are taking other drugs
- heart disease
- high blood pressure
- thyroid disease
- diabetes

When using this product

- excitability may occur, especially in children
- may cause marked drowsiness
- avoid alcoholic drinks
- may cause or aggravate constipation
- alcohol, sedatives, and tranquilizers may increase drowsiness effect

Stop use and ask a doctor if

- nervousness, dizziness, or sleeplessness occur
- cough or nasal congestion persists for more than 1 week, tends to recur, or is accompanied by a fever, rash or persistent headache. These could be signs of a serious condition.
- new symptoms occur

PREGNANCY OR BREAST FEEDING

If pregnant or breastfeeding ask a health professional before use

Keep out of reach of children. In case of overdose, get medical help or contact a Poison Control Center right away

Do not use this product

if you are now taking a prescription monoamine oxidase inhibitor (MAOI) (certain drugs for depression, psychiatric, or emotional

conditions, or Parkinson’s disease), or for 2 weeks after stopping the MAOI drug. If you do not know if your prescription drug contains an MAOI, ask a doctor or pharmacist before taking this product.

Directions

Adults 12 and over: 10 mL every 4-6 hours

Not to exceed 60 mL in 24 hours or as directed by a doctor

Children 6-12: 5 mL every 4 hours,

Not to exceed 30 mL in 24 hrs or as directed by a doctor

Children under 6: Consult a doctor

Other information

Store at room temperature 15°C-30°C (59°F-86°F)

Questions? Comments? Serious side effects associated with use of this product may be reported to this number. Call 1-800-882-1041
Mon. - Fri. (8 a.m. to 5 p.m. CST).

Inactive ingredients

Inactive ingredients Cherry flavor, citric acid, glycerin, propylene glycol, purified water,sodium benzoate, sodium citrate, sorbitol solution, sucralose.